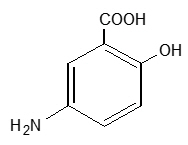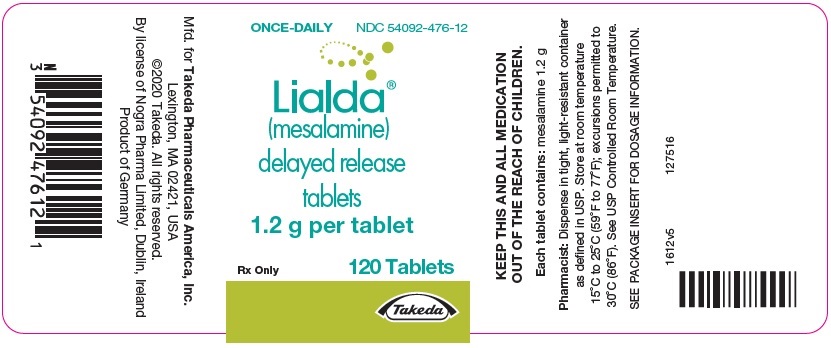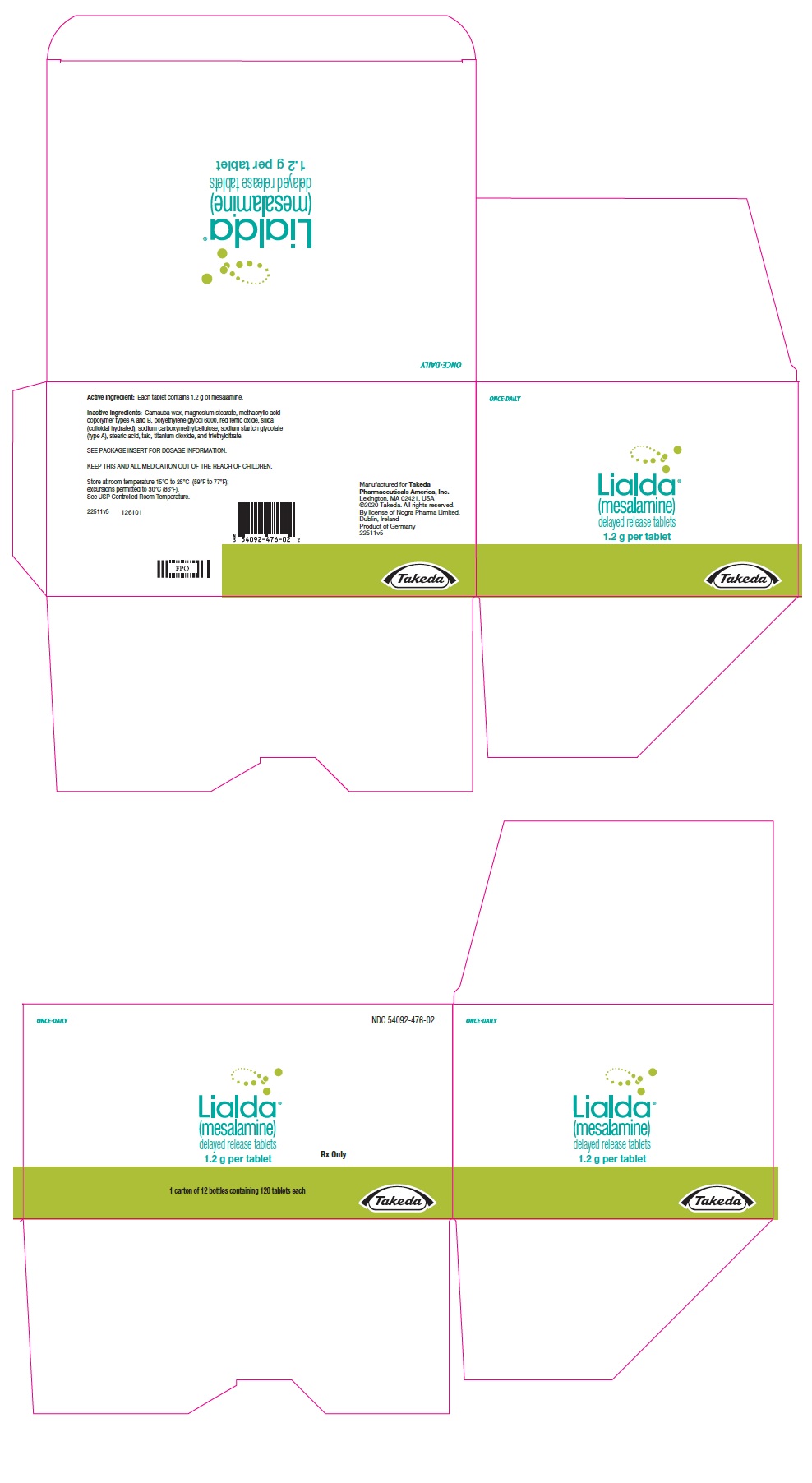 DRUG LABEL: Lialda
NDC: 54092-476 | Form: TABLET, DELAYED RELEASE
Manufacturer: Takeda Pharmaceuticals America, Inc.
Category: prescription | Type: HUMAN PRESCRIPTION DRUG LABEL
Date: 20251216

ACTIVE INGREDIENTS: MESALAMINE 1.2 g/1 1
INACTIVE INGREDIENTS: CARBOXYMETHYLCELLULOSE SODIUM, UNSPECIFIED; CARNAUBA WAX; STEARIC ACID; SILICON DIOXIDE; SODIUM STARCH GLYCOLATE TYPE A POTATO; TALC; MAGNESIUM STEARATE; METHACRYLIC ACID - METHYL METHACRYLATE COPOLYMER (1:1); TRIETHYL CITRATE; TITANIUM DIOXIDE; FERRIC OXIDE RED; POLYETHYLENE GLYCOL 6000; METHACRYLIC ACID - METHYL METHACRYLATE COPOLYMER (1:2)

HIGHLIGHTS OF PRESCRIBING INFORMATION

These highlights do not include all the information needed to use LIALDA safely and effectively. See full prescribing information for LIALDA.
LIALDA® (mesalamine) delayed-release tablets, for oral use
Initial U.S. Approval: 1987

RECENT MAJOR CHANGES

Warnings and Precautions, Renal Impairment (5.1) | 11/2022

1 INDICATIONS AND USAGE

LIALDA is an aminosalicylate indicated for the:

- induction and maintenance of remission in adult patients with mildly to moderately active ulcerative colitis. (1)
- treatment of mildly to moderately active ulcerative colitis in pediatric patients weighing at least 24 kg. (1)

2 DOSAGE AND ADMINISTRATION

Administration Instructions

- Evaluate renal function prior to initiation of LIALDA and periodically while on therapy. (2, 5.1)
- Swallow LIALDA tablets whole; do not split or crush. (2)
- Administer LIALDA tablets with food. (2)
- Drink an adequate amount of fluids. (2, 5.8)

Recommended Dosage in Adults

- For induction of remission: 2.4 g to 4.8 g (two to four 1.2-g tablets) once daily. (2)
- For maintenance of remission: 2.4 g (two 1.2-g tablets) once daily. (2)

Recommended Dosage in Pediatric Patients

- The recommended dosage for treatment of mildly to moderately active ulcerative colitis in pediatric patients weighing at least 24 kg who can swallow tablets whole is shown below: (2)

Weight of Pediatric Patient | Once Daily LIALDA Dosage
Weight of Pediatric Patient | Week 0 to Week 8 | After Week 8
24 kg to 35 kg | 2.4 g (two 1.2-g tablets) | 1.2 g (one 1.2-g tablet)
Greater than 35 kg to 50 kg | 3.6 g (three 1.2-g tablets) | 2.4 g (two 1.2-g tablets)
Greater than 50 kg | 4.8 g (four 1.2-g tablets) | 2.4 g (two 1.2-g tablets)

3 DOSAGE FORMS AND STRENGTHS

Delayed-Release Tablets: 1.2 g (3)

4 CONTRAINDICATIONS

Known or suspected hypersensitivity to salicylates or aminosalicylates or to any of the ingredients of LIALDA. (4)

5 WARNINGS AND PRECAUTIONS

- Renal Impairment: Assess renal function at the beginning of treatment and periodically during treatment. Evaluate the risks and benefits of LIALDA in patients with known renal impairment or taking nephrotoxic drugs. Discontinue LIALDA if renal function deteriorates while on therapy. (5.1, 7.1, 8.6)
- Mesalamine-Induced Acute Intolerance Syndrome: Symptoms may be difficult to distinguish from an ulcerative colitis exacerbation. Monitor for worsening symptoms while on treatment. Discontinue treatment if acute intolerance syndrome is suspected. (5.2)
- Hypersensitivity Reactions, including myocarditis and pericarditis: Evaluate patients immediately and discontinue LIALDA if a hypersensitivity reaction is suspected. (5.3)
- Hepatic Failure: Evaluate the risks and benefits of using LIALDA in patients with known liver impairment. (5.4)
- Severe Cutaneous Adverse Reactions: Discontinue at the first signs or symptoms of severe cutaneous adverse reactions or other signs of hypersensitivity and consider further evaluation. (5.5)
- Upper Gastrointestinal Tract Obstruction: Avoid in patients with pyloric stenosis or other organic or functional obstruction. (5.6)
- Photosensitivity: Advise patients with pre-existing skin conditions to avoid sun exposure, wear protective clothing, and use a broad-spectrum sunscreen when outdoors. (5.7)
- Nephrolithiasis: Cases of nephrolithiasis have been reported with the use of mesalamine. Mesalamine-containing stones are undetectable by standard radiography or computed tomography (CT). Ensure adequate hydration during treatment. (5.8)
- Interference With Laboratory Tests: Use of mesalamine may lead to spuriously elevated test results when measuring urinary normetanephrine by liquid chromatography with electrochemical detection. (5.9)

6 ADVERSE REACTIONS

Most common adverse reactions in:

- adults (≥2%) are headache, flatulence, liver function test abnormal, abdominal pain, and diarrhea. (6.1)
- pediatric patients (≥5%) are abdominal pain, upper respiratory tract infection, vomiting, anemia, headache, and viral infection. (6.1)

To report SUSPECTED ADVERSE REACTIONS, contact Takeda Pharmaceuticals at 1-800-828-2088 or FDA at 1-800-FDA-1088 or www.fda.gov/medwatch.

7 DRUG INTERACTIONS

- Nephrotoxic Agents including NSAIDs: Increased risk of nephrotoxicity; monitor for changes in renal function and mesalamine-related adverse reactions. (7.1)
- Azathioprine or 6-Mercaptopurine: Increased risk of blood dyscrasias; monitor complete blood cell counts and platelet counts. (7.2)

8 USE IN SPECIFIC POPULATIONS

Geriatric Patients: Increased risk of blood dyscrasias; monitor complete blood cell counts and platelet counts. (8.5)

FULL PRESCRIBING INFORMATION

1 INDICATIONS AND USAGE

LIALDA is indicated for the:

- induction and maintenance of remission in adult patients with mildly to moderately active ulcerative colitis.
- treatment of mildly to moderately active ulcerative colitis in pediatric patients weighing at least 24 kg.

2 DOSAGE AND ADMINISTRATION

Administration Instructions

- Evaluate renal function prior to initiation of LIALDA and periodically while on therapy.
- Swallow LIALDA tablets whole; do not split or crush.
- Administer LIALDA tablets with food [see Clinical Pharmacology (12.3)].
- Drink an adequate amount of fluids [see Warnings and Precautions (5.8)].

Adults

- The recommended dosage for the induction of remission in adult patients with mildly to moderately active ulcerative colitis is 2.4 g to 4.8 g (two to four 1.2-g tablets) taken once daily.
- The recommended dosage for the maintenance of remission is 2.4 g (two 1.2-g tablets) taken once daily.

Pediatric Patients

The recommended dosage for treatment of mildly to moderately active ulcerative colitis in pediatric patients weighing at least 24 kg who can swallow tablets whole is shown in Table 1:

Table 1: Recommended Dosage of LIALDA for the Treatment of Mildly to Moderately Active Ulcerative Colitis in Pediatric Patients Weighing at least 24 kg
Weight of Pediatric Patient | Once Daily LIALDA Dosage
Weight of Pediatric Patient | Week 0 to Week 8 | After Week 8
24 kg to 35 kg | 2.4 g (two 1.2-g tablets) | 1.2 g (one 1.2-g tablet)
Greater than 35 kg to 50 kg | 3.6 g (three 1.2-g tablets) | 2.4 g (two 1.2-g tablets)
Greater than 50 kg | 4.8 g (four 1.2-g tablets) | 2.4 g (two 1.2-g tablets)

3 DOSAGE FORMS AND STRENGTHS

The red-brown ellipsoidal delayed-release tablet containing 1.2 g mesalamine is debossed on one side and imprinted with S476.

4 CONTRAINDICATIONS

LIALDA is contraindicated in patients with known or suspected hypersensitivity to salicylates, aminosalicylates, or to any of the ingredients of LIALDA [see Warnings and Precautions (5.3), Adverse Reactions (6.2), Description (11)].

5 WARNINGS AND PRECAUTIONS

5.1 Renal Impairment

Renal impairment, including minimal change disease, acute and chronic interstitial nephritis, and, rarely, renal failure, has been reported in patients given products such as LIALDA that contain mesalamine or are converted to mesalamine. In animal studies, the kidney was the principal organ of mesalamine toxicity [see Adverse Reactions (6.2), Nonclinical Toxicology (13.2)].

Evaluate renal function prior to initiation of LIALDA therapy and periodically while on therapy. Evaluate the risks and benefits of using LIALDA in patients with known renal impairment, history of renal disease, or taking concomitant nephrotoxic drugs. Discontinue LIALDA if renal function deteriorates while on therapy [see Drug Interactions (7.1), Use in Specific Populations (8.6)].

5.2 Mesalamine-Induced Acute Intolerance Syndrome

Mesalamine has been associated with an acute intolerance syndrome that may be difficult to distinguish from an exacerbation of ulcerative colitis. Although the exact frequency of occurrence has not been determined, it has occurred in 3% of patients in controlled clinical trials of mesalamine or sulfasalazine. Symptoms include cramping, acute abdominal pain, and bloody diarrhea, and sometimes fever, headache, and rash. Monitor patients closely for worsening of these symptoms while on treatment. If acute intolerance syndrome is suspected, promptly discontinue treatment with LIALDA.

5.3 Hypersensitivity Reactions

Hypersensitivity reactions have been reported in patients taking sulfasalazine. Some of these patients may have a similar reaction to LIALDA tablets or to other compounds that contain or are converted to mesalamine.

As with sulfasalazine, mesalamine-induced hypersensitivity reactions may present as internal organ involvement, including myocarditis, pericarditis, nephritis, hepatitis, pneumonitis, and hematologic abnormalities. Evaluate patients immediately if signs or symptoms of a hypersensitivity reaction are present. Discontinue LIALDA if an alternative etiology for the signs or symptoms cannot be established.

5.4 Hepatic Failure

There have been reports of hepatic failure in patients with pre-existing liver disease who have been administered mesalamine. Evaluate the risks and benefits of using LIALDA in patients with known liver impairment.

5.5 Severe Cutaneous Adverse Reactions

Severe cutaneous adverse reactions, such as Stevens-Johnson syndrome (SJS) and toxic epidermal necrolysis (TEN), drug reaction with eosinophilia and systemic symptoms (DRESS), and acute generalized exanthematous pustulosis (AGEP) have been reported with the use of mesalamine [see Adverse Reactions (6.2)]. Discontinue LIALDA at the first appearance of signs or symptoms of severe cutaneous adverse reactions or other signs of hypersensitivity and consider further evaluation.

5.6 Upper Gastrointestinal Tract Obstruction

Pyloric stenosis or other organic or functional obstruction in the upper gastrointestinal tract may cause prolonged gastric retention of LIALDA, which would delay mesalamine release in the colon. Avoid LIALDA in patients at risk of upper gastrointestinal tract obstruction.

5.7 Photosensitivity

Patients with pre-existing skin conditions such as atopic dermatitis and atopic eczema have reported more severe photosensitivity reactions. Advise patients to avoid sun exposure, wear protective clothing, and use a broad-spectrum sunscreen when outdoors.

5.8 Nephrolithiasis

Cases of nephrolithiasis have been reported with the use of mesalamine, including stones with a 100% mesalamine content. Mesalamine-containing stones are radiotransparent and undetectable by standard radiography or computed tomography (CT). Ensure adequate hydration during treatment with LIALDA.

5.9 Interference with Laboratory Tests

Use of LIALDA may lead to spuriously elevated test results when measuring urinary normetanephrine by liquid chromatography with electrochemical detection because of the similarity in the chromatograms of normetanephrine and the main metabolite of mesalamine, N-acetyl-5-aminosalicylic acid (N-Ac-5-ASA). Consider an alternative, selective assay for normetanephrine.

6 ADVERSE REACTIONS

The following clinically significant adverse reactions are described elsewhere in labeling:

- Renal impairment, including renal failure [see Warnings and Precautions (5.1)]
- Mesalamine-induced acute intolerance syndrome [see Warnings and Precautions (5.2)]
- Hypersensitivity reactions [see Warnings and Precautions (5.3)]
- Hepatic failure [see Warnings and Precautions (5.4)]
- Severe cutaneous adverse reactions [see Warnings and Precautions (5.5)]
- Upper gastrointestinal tract obstruction [see Warnings and Precautions (5.6)]
- Photosensitivity [see Warnings and Precautions (5.7)]
- Nephrolithiasis [see Warnings and Precautions (5.8)]

6.1 Clinical Trials Experience

Because clinical trials are conducted under widely varying conditions, adverse reaction rates observed in the clinical trials of a drug cannot be directly compared to rates in the clinical trials of another drug and may not reflect the rates observed in practice.

Adults

Induction

The most common adverse reactions occurring in at least 1% of LIALDA- or placebo-treated adult patients with mildly to moderately active ulcerative colitis in two eight-week, randomized, double-blind, placebo-controlled trials (Study 1 and Study 2) [see Clinical Studies (14.1)] are listed in Table 2.

Table 2: Adverse Reactions [Reported in at least 1% of patients in at least one LIALDA group and greater than placebo] in Two Eight-Week, Placebo-Controlled Trials of Induction Therapy (Study 1 and Study 2) in Adults with Mildly to Moderately Active Ulcerative Colitis
Adverse Reaction | LIALDA 2.4 g once daily | LIALDA 4.8 g once daily | Placebo
Adverse Reaction | (n=177) | (n=179) | (n=179)
Headache | 6% | 3% | <1%
Flatulence | 4% | 3% | 3%
Liver Function Test Abnormal | <1% | 2% | 1%
Alopecia | 0 | 1% | 0
Pruritus | <1% | 1% | 1%

Pancreatitis occurred in less than 1% of patients during induction in clinical trials and resulted in discontinuation of therapy with LIALDA in patients experiencing this event.

Maintenance of Remission

A LIALDA dosage of 2.4 g/day, administered as either 1.2 g twice daily or 2.4 g once daily, was evaluated for safety in three maintenance trials in patients with mildly to moderately active ulcerative colitis: a 6-month double-blind, active-controlled study (Study 3) [see Clinical Studies (14.1)] and two 12- to 14-month open-label studies. The most common adverse reactions with LIALDA in these maintenance trials are listed in Table 3.

Table 3: Adverse Reactions [Reported in at least 1% of patients] in Three Trials of Maintenance of Remission in Adults with Ulcerative Colitis
 | LIALDA 2.4 g/day [Administered either as 1.2 g twice daily or 2.4 g once daily]
 | (n=1082)
Adverse Reaction | %
Headache | 3%
Liver function test abnormal | 2%
Abdominal pain | 2%
Diarrhea | 2%
Abdominal distension | 1%
Abdominal pain upper | 1%
Dyspepsia | 1%
Back pain | 1%
Rash | 1%
Arthralgia | 1%
Fatigue | 1%
Hypertension | 1%

The following adverse reactions, presented by body system, were reported in less than 1% of LIALDA-treated patients with ulcerative colitis in either induction or maintenance trials:

Cardiac Disorder: tachycardia

Ear and Labyrinth Disorders: ear pain

Gastrointestinal Disorders: abdominal distention, colitis, diarrhea, flatulence, nausea, pancreatitis, rectal polyp, vomiting

General Disorders and Administrative Site Disorders: asthenia, face edema, fatigue, pyrexia

Investigations: decreased platelet count

Musculoskeletal and Connective Tissue Disorders: arthralgia, back pain

Nervous System Disorders: dizziness, somnolence, tremor

Respiratory, Thoracic and Mediastinal Disorders: pharyngolaryngeal pain

Skin and Subcutaneous Tissue Disorders: acne, prurigo, rash, alopecia, pruritus, urticaria

Vascular Disorders: hypertension, hypotension

Pediatrics

LIALDA was evaluated in 105 pediatric patients 5 through 17 years of age with mildly to moderately active ulcerative colitis [see Clinical Studies (14.2)]. The adverse reaction profile was similar to that of adults. The most common adverse reactions reported in at least 5% of pediatric patients treated with LIALDA were: abdominal pain, upper respiratory tract infection, vomiting, anemia, headache, and viral infection.

6.2 Postmarketing Experience

The following adverse reactions have been identified during post-approval use of LIALDA or other mesalamine-containing products. Because these reactions are reported voluntarily from a population of uncertain size, it is not always possible to reliably estimate their frequency or establish a causal relationship to drug exposure.

Body as a Whole: lupus-like syndrome, drug fever

Cardiac Disorders: pericarditis, pericardial effusion, myocarditis [see Warnings and Precautions (5.3)]

Gastrointestinal: cholecystitis, gastritis, gastroenteritis, gastrointestinal bleeding, perforated peptic ulcer

Hepatic: jaundice, cholestatic jaundice, hepatitis, liver necrosis, liver failure, hepatotoxicity, Kawasaki-like syndrome including changes in liver enzymes

Hematologic: agranulocytosis, aplastic anemia

Immune System Disorders: anaphylactic reaction, angioedema

Musculoskeletal and Connective Tissue Disorders: myalgia, lupus-like syndrome

Neurological/Psychiatric: peripheral neuropathy, Guillain-Barré syndrome, transverse myelitis, intracranial hypertension

Renal Disorders: renal failure, interstitial nephritis, nephrogenic diabetes insipidus, nephrolithiasis [see Warnings and Precautions (5.1, 5.8)]

- Urine discoloration occurring ex-vivo caused by contact of mesalamine, including inactive metabolite, with surfaces or water treated with hypochlorite-containing bleach

Respiratory, Thoracic and Mediastinal Disorders: interstitial lung disease, hypersensitivity pneumonitis (including interstitial pneumonitis, allergic alveolitis, eosinophilic pneumonitis), pleurisy/pleuritis

Skin: psoriasis, pyoderma gangrenosum, erythema nodosum, photosensitivity, SJS/TEN, DRESS, and AGEP [see Warnings and Precautions (5.5)]

Urogenital: reversible oligospermia

7 DRUG INTERACTIONS

7.1 Nephrotoxic Agents, Including Non-Steroidal Anti-Inflammatory Drugs

The concurrent use of mesalamine with known nephrotoxic agents, including non-steroidal anti-inflammatory drugs (NSAIDs), may increase the risk of nephrotoxicity. Monitor patients taking nephrotoxic drugs for changes in renal function and mesalamine-related adverse reactions [see Warnings and Precautions (5.1)].

7.2 Azathioprine and 6-Mercaptopurine

The concurrent use of mesalamine with azathioprine or 6-mercaptopurine and/or any other drugs known to cause myelotoxicity may increase the risk for blood disorders, bone marrow failure, and associated complications. If concomitant use of LIALDA and azathioprine or 6-mercaptopurine cannot be avoided, monitor blood tests, including complete blood cell counts and platelet counts.

7.3 Interference with Urinary Normetanephrine Measurements

Use of LIALDA may lead to spuriously elevated test results when measuring urinary normetanephrine by liquid chromatography with electrochemical detection [see Warnings and Precautions (5.9)]. Consider an alternative, selective assay for normetanephrine.

8 USE IN SPECIFIC POPULATIONS

8.1 Pregnancy

Risk Summary

Published data from meta-analyses, cohort studies, and case series on the use of mesalamine during pregnancy have not reliably informed an association with mesalamine and major birth defects, miscarriage, or adverse maternal or fetal outcomes (see Data). There are adverse effects on maternal and fetal outcomes associated with ulcerative colitis in pregnancy (see Clinical Considerations).

In animal reproduction studies, there were no adverse developmental outcomes with administration of oral mesalamine during organogenesis to pregnant rats and rabbits at doses 1.8 and 2.9 times, respectively, the maximum recommended human dose (see Data).

The estimated background risk of major birth defects and miscarriage for the indicated populations is unknown. All pregnancies have a background risk of birth defect, loss, or other adverse outcomes. In the U.S. general population, the estimated background risk of major birth defects and miscarriages in clinically recognized pregnancies is 2% to 4% and 15% to 20%, respectively.

Clinical Considerations

Disease-associated maternal and embryo/fetal risk

Published data suggest that increased disease activity is associated with the risk of developing adverse pregnancy outcomes in women with ulcerative colitis. Adverse pregnancy outcomes include preterm delivery (before 37 weeks of gestation), low birth weight (less than 2500 g) infants, and small for gestational age at birth.

Data

Human Data

Published data from meta-analyses, cohort studies, and case series on the use of mesalamine during early pregnancy (first trimester) and throughout pregnancy have not reliably informed an association of mesalamine and major birth defects, miscarriage, or adverse maternal or fetal outcomes. There is no clear evidence that mesalamine exposure in early pregnancy is associated with an increased risk of major congenital malformations, including cardiac malformations. Published epidemiologic studies have important methodological limitations which hinder interpretation of the data, including inability to control for confounders, such as underlying maternal disease, maternal use of concomitant medications, and missing information on the dose and duration of use for mesalamine products.

Animal Data

Reproduction studies with mesalamine during organogenesis have been performed in rats at doses up to 1000 mg/kg/day (1.8 times the maximum recommended human dose based on a body surface area comparison) and rabbits at doses up to 800 mg/kg/day (2.9 times the maximum recommended human dose based on a body surface area comparison) and have revealed no evidence of harm to the fetus due to mesalamine.

8.2 Lactation

Risk Summary

Data from published literature report the presence of mesalamine and its metabolite, N-acetyl-5-aminosalicylic acid in human milk in small amounts with relative infant doses (RID) of 0.1% or less for mesalamine (see Data). There are case reports of diarrhea in breastfed infants exposed to mesalamine (see Clinical Considerations). There is no information on the effects of the drug on milk production. The lack of clinical data during lactation precludes a clear determination of the risk of LIALDA to an infant during lactation; therefore, the developmental and health benefits of breastfeeding should be considered along with the mother's clinical need for LIALDA and any potential adverse effects on the breastfed child from LIALDA or from the underlying maternal condition.

Clinical Considerations

Advise the caregiver to monitor the breastfed infant for diarrhea.

Data

In published lactation studies, maternal mesalamine doses from various oral and rectal formulations and products ranged from 500 mg to 4.8 g daily. The average concentration of mesalamine in milk ranged from non-detectable to 0.5 mg/L. The average concentration of N-acetyl-5-aminosalicylic acid in milk ranged from 0.2 to 9.3 mg/L. Based on these concentrations, estimated infant daily dosages for an exclusively breastfed infant are 0 to 0.075 mg/kg/day (RID 0% to 0.1%) of mesalamine and 0.03 to 1.4 mg/kg/day of N-acetyl-5-aminosalicylic acid.

8.4 Pediatric Use

The safety and effectiveness of LIALDA have been established for the treatment of mildly to moderately active ulcerative colitis in pediatric patients weighing at least 24 kg. Use of LIALDA in this population is supported by evidence from adequate and well-controlled trials in adults, a multicenter, randomized, double-blind, parallel group trial in 105 pediatric patients 5 to 17 years of age, and additional pharmacokinetic analyses. The safety profile in pediatric patients was similar to that observed in adults [see Adverse Reactions (6.1), Clinical Pharmacology (12.3), Clinical Studies (14.2)].

The safety and effectiveness of LIALDA have not been established in patients weighing less than 24 kg.

8.5 Geriatric Use

Clinical trials of LIALDA did not include sufficient numbers of patients aged 65 years and over to determine whether they respond differently from younger patients. Reports from uncontrolled clinical studies and postmarketing reporting systems suggested a higher incidence of blood dyscrasias (i.e., agranulocytosis, neutropenia, and pancytopenia) in patients who were 65 years or older who were taking mesalamine-containing products such as LIALDA compared to younger patients. Monitor complete blood cell counts and platelet counts in elderly patients during treatment with LIALDA.

Systemic exposures are increased in elderly subjects [see Clinical Pharmacology (12.3)].

In general, consider the greater frequency of decreased hepatic, renal, or cardiac function, and of concomitant disease or other drug therapy in elderly patients when prescribing LIALDA. Consider starting at the low end of the dosing range for induction in elderly patients [see Dosage and Administration (2), Use in Specific Populations (8.6)].

8.6 Renal Impairment

Mesalamine is known to be substantially excreted by the kidney, and the risk of toxic reactions may be greater in patients with impaired renal function. Evaluate renal function in all patients prior to initiation and periodically while on LIALDA therapy. Monitor patients with known renal impairment or history of renal disease or taking nephrotoxic drugs for decreased renal function and mesalamine-related adverse reactions. Discontinue LIALDA if renal function deteriorates while on therapy [see Warnings and Precautions (5.1), Adverse Reactions (6.2), Drug Interactions (7.1)].

10 OVERDOSAGE

LIALDA is an aminosalicylate, and symptoms of salicylate toxicity may include nausea, vomiting, abdominal pain, tachypnea, hyperpnea, tinnitus, and neurologic symptoms (headache, dizziness, confusion, seizures). Severe intoxication with salicylates may lead to electrolyte and blood pH imbalance, and potentially end organ (e.g., renal and liver) damage.

There is no specific known antidote for mesalamine overdose; however, conventional therapy for salicylate toxicity may be beneficial in the event of acute overdosage and may include gastrointestinal tract decontamination to prevent further absorption. Correct fluid and electrolyte imbalance by the administration of appropriate intravenous therapy and maintain adequate renal function.

LIALDA is a pH-dependent, delayed-release product and this factor should be considered when treating a suspected overdose.

11 DESCRIPTION

Each LIALDA delayed-release tablet for oral administration contains 1.2 g 5-aminosalicylic acid (5-ASA; mesalamine), an anti-inflammatory agent. Mesalamine also has the chemical name 5-amino-2-hydroxybenzoic acid and its structural formula is:

Molecular formula:

C7H7NO3

Molecular weight:

153.14

The tablet is coated with a pH-dependent polymer film, which breaks down at or above pH 6.8, normally in the terminal ileum where mesalamine then begins to be released from the tablet core. The tablet core contains mesalamine with hydrophilic and lipophilic excipients and provides for extended release of mesalamine.

The inactive ingredients of LIALDA are sodium carboxymethylcellulose, carnauba wax, stearic acid, silica (colloidal hydrated), sodium starch glycolate (type A), talc, magnesium stearate, methacrylic acid copolymer types A and B, triethylcitrate, titanium dioxide, red ferric oxide, and polyethylene glycol 6000.

12 CLINICAL PHARMACOLOGY

12.1 Mechanism of Action

The mechanism of action of mesalamine is not fully understood, but it appears to have a topical anti-inflammatory effect on the colonic epithelial cells. Mucosal production of arachidonic acid metabolites, both through the cyclooxygenase and lipoxygenase pathways, is increased in patients with ulcerative colitis, and it is possible that mesalamine diminishes inflammation by blocking cyclooxygenase and inhibiting prostaglandin production in the colon.

12.3 Pharmacokinetics

Absorption

The total absorption of mesalamine from LIALDA 2.4 g or 4.8 g given once daily for 14 days to healthy subjects was found to be approximately 21% to 22% of the administered dose.

Gamma-scintigraphy studies have shown that a single dose of LIALDA 1.2 g (one tablet) passed intact through the upper gastrointestinal tract of fasted healthy subjects. Scintigraphic images showed a trail of radio-labeled tracer in the colon, suggesting that mesalamine had distributed through this region of the gastrointestinal tract.

In a single-dose study, LIALDA 1.2 g, 2.4 g, and 4.8 g were administered in the fasted state to healthy subjects. Plasma concentrations of mesalamine were detectable after 2 hours and reached a maximum by 9-12 hours on average for the doses studied. The pharmacokinetic parameters are highly variable among subjects (Table 4). Mesalamine systemic exposure in terms of area under the plasma concentration-time curve (AUC) was slightly more than dose proportional between 1.2 g and 4.8 g LIALDA. Maximum plasma concentrations (Cmax) of mesalamine increased approximately dose proportionately between 1.2 g and 2.4 g and sub-proportionately between 2.4 g and 4.8 g of LIALDA, with the dose normalized value at 4.8 g representing, on average, 74% of that at 2.4 g based on geometric means.

Table 4: Mean (SD) Pharmacokinetic Parameters for Mesalamine Following Single-Dose Administration of LIALDA Under Fasting Conditions
Parameter [Arithmetic mean of parameter values are presented except for Tmax and Tlag.] of Mesalamine | LIALDA 1.2 g (N=47) | LIALDA 2.4 g (N=48) | LIALDA 4.8 g (N=48)
AUC0-t (ng∙h/mL) | 9039 [N=43,] (5054) | 20538 (12980) | 41434 (26640)
AUC0-∞ (ng∙h/mL) | 9578 [N=27,] (5214) | 21084 (13185) | 44775 [N=36,] (30302)
Cmax (ng/mL) | 857 (638) | 1595 (1484) | 2154 (1140)
Tmax [Median (min, max),] (h) | 9.0 [N=46,] (4.0-32.1) | 12.0 (4.0-34.1) | 12.0 (4.0-34.0)
Tlag (h) | 2.0 (0-8.0) | 2.0 (1.0-4.0) | 2.0 (1.0-4.0)
T1/2 (h) (Terminal Phase) | 8.56 (6.38) | 7.05 [N=33] (5.54) | 7.25 (8.32)

Food Effects

Administration of a single dose of LIALDA 4.8 g with a high-fat meal resulted in further delay in absorption, and plasma concentrations of mesalamine were detectable 4 hours following dosing. However, a high-fat meal increased systemic exposure of mesalamine (mean Cmax: increased 91%; mean AUC: increased 16%) compared to results in the fasted state. LIALDA was administered with food in the controlled clinical trials [see Dosage and Administration (2)].

In a single- and multiple-dose pharmacokinetic study of LIALDA, 2.4 g or 4.8 g was administered once daily with standard meals to 28 healthy subjects per dose group. Plasma concentrations of mesalamine were detectable after 4 hours and were maximal by 8 hours after the single dose. Steady state was achieved generally by 2 days after dosing. Mean AUC at steady state was only modestly greater (1.1- to 1.4-fold) than predictable from single dose pharmacokinetics.

Distribution

Mesalamine is approximately 43% bound to plasma proteins at the concentration of 2.5 mcg/mL.

Elimination

Metabolism

The only major metabolite of mesalamine (5-aminosalicylic acid) is N-acetyl-5-aminosalicylic acid. Its formation is brought about by N-acetyltransferase (NAT) activity in the liver and intestinal mucosa cells, principally by NAT-1.

Excretion

Excretion of mesalamine is mainly via the renal route following metabolism to N-acetyl-5-aminosalicylic acid (acetylation); however, there is also limited excretion of the parent drug in urine. Of the approximately 21% to 22% of the dose absorbed, less than 8% of the dose was excreted unchanged in the urine after 24 hours, compared with greater than 13% for N-acetyl-5-aminosalicylic acid. The mean renal clearance (CLR) in adults ranged from 1.8 L/h to 2.9 L/h following single dose administration and ranged from 5.5 L/h to 6.4 L/h after a multiple dosing for 14 days. The apparent terminal half-lives for mesalamine and its major metabolite after administration of LIALDA 2.4 g and 4.8 g were, on average, 7 to 9 hours and 8 to 12 hours, respectively.

Systemic exposures in adult subjects were inversely correlated with renal function as assessed by estimated creatinine clearance [see Use in Specific Populations (8.6)].

Specific Populations

Geriatric Patients

In a single-dose pharmacokinetic study of LIALDA, 4.8 g was administered in the fasted state to 71 healthy male and female subjects (28 young (18-35 years); 28 elderly (65-75 years); 15 elderly (>75 years)). Increased age resulted in increased systemic exposure (approximately 2-fold in Cmax) to mesalamine and its metabolite N-acetyl-5-aminosalicylic acid. Increased age resulted in a slower apparent elimination of mesalamine, though there was high between-subject variability.

Table 5: Mean (SD) Pharmacokinetic Parameters for Mesalamine Following Single-Dose Administration of LIALDA 4.8 g under Fasting Conditions to Young and Elderly Subjects
Parameter of 5-ASA | Young Subjects (18 to 35 years) (N=28) | Elderly Subjects (65 to 75 years) (N=28) | Elderly Subjects (75 years and older) (N=15)
AUC0-t (ng∙h/mL) | 51570 (23870) | 73001 (42608) | 65820 (25283)
AUC0-∞ (ng∙h/mL) | 58057 [N=15,] (22429) | 89612 [N=16,] (40596) | 63067 [N=13,] (22531)
Cmax (ng/mL) | 2243 (1410) | 4999 (4381) | 4832 (4383)
tmax [Median (min-max)] (h) | 22.0 (5.98–48.0) | 12.5 (4.00–36.0) | 16.0 (4.00–26.0)
tlag (h) | 2 (1–6) | 2 (1–4) | 2 (2–4)
t½ (h), terminal phase | 5.68 (2.83) | 9.68 (7.47) | 8.67 (5.84)
Renal clearance (L/h) | 2.05 (1.33) | 2.04 (1.16) | 2.13 (1.20)
Arithmetic mean (SD) data are presented, N = Number of subjects; 5-ASA = 5-aminosalicylic acid

Pediatric Patients

In pediatric patients 5 years to 17 years of age diagnosed with ulcerative colitis, systemic exposure of mesalamine, as measured by mean AUCss and Cmax,ss, increased in a dose-proportional manner between 30 and 60 mg/kg/day of LIALDA and increased in a sub-proportional between 60 and 100 mg/kg/day doses. Pharmacokinetic parameters had moderate to high inter-subject variability with CV% ranging from 36% to 52% in pediatric patients.

The overall systemic exposure of mesalamine following oral administration of 4.8 g once daily for 7 days in a limited number of pediatric patients 5 years to 17 years of age (AUC range of 30,556 to 50,388 ng∙hr/mL, n=3) was in similar range to that was observed in the healthy adults (AUC of 41,434 ± 26,640 ng∙hr/mL, n=48) after single dose administration.

The mean renal clearance (CLR) of mesalamine in pediatric patients (range from approximately 5.0 to 6.5 L/h) seems to be similar to that observed with healthy adult subjects after multiple dose administration.

Drug Interaction Studies

The potential effect of LIALDA (4.8 g given once daily) on the pharmacokinetics of four commonly used antibiotics were evaluated in healthy subjects. The four antibiotics studied and their dosing regimens were as follows: amoxicillin (single 500-mg dose), ciprofloxacin XR (single 500-mg dose), metronidazole (750 mg twice daily for 3.5 days), and sulfamethoxazole/trimethoprim (800 mg/160 mg twice daily for 3.5 days). The change in Cmax and AUC of amoxicillin, ciprofloxacin, and metronidazole when they were co-administered with LIALDA were all 3% or less. There was an increase of 12% in Cmax and an increase of 15% in AUC of sulfamethoxazole when sulfamethoxazole/trimethoprim was coadministered with LIALDA. Coadministration of LIALDA did not result in clinically significant changes in the pharmacokinetics of any of the four antibiotics.

13 NONCLINICAL TOXICOLOGY

13.1 Carcinogenesis, Mutagenesis, Impairment of Fertility

Carcinogenesis

In a 104-week dietary carcinogenicity study in CD-1 mice, mesalamine at doses up to 2500 mg/kg/day was not tumorigenic. This dose is 2.2 times the maximum recommended human dose (based on a body surface area comparison) of LIALDA. Furthermore, in a 104-week dietary carcinogenicity study in Wistar rats, mesalamine up to a dose of 800 mg/kg/day was not tumorigenic. This dose is 1.4 times the recommended human dose (based on a body surface area comparison) of LIALDA.

Mutagenesis

No evidence of mutagenicity was observed in an in vitro Ames test or an in vivo mouse micronucleus test.

Impairment of Fertility

No effects on fertility or reproductive performance were observed in male or female rats at oral doses of mesalamine up to 400 mg/kg/day (0.7 times the maximum recommended human dose based on a body surface area comparison).

13.2 Animal Toxicology and/or Pharmacology

In animal studies with mesalamine, a 13-week oral toxicity study in mice and 13-week and 52-week oral toxicity studies in rats and cynomolgus monkeys have shown the kidney to be the major target organ of mesalamine toxicity. Oral daily doses of 2400 mg/kg in mice and 1150 mg/kg in rats produced renal lesions including granular and hyaline casts, tubular degeneration, tubular dilation, renal infarct, papillary necrosis, tubular necrosis, and interstitial nephritis. In cynomolgus monkeys, oral daily doses of 250 mg/kg or higher produced nephrosis, papillary edema, and interstitial fibrosis.

14 CLINICAL STUDIES

14.1 Adults with Mildly to Moderately Active Ulcerative Colitis

Induction of Remission

Two similarly designed, randomized, double-blind, placebo-controlled trials (Study 1, NCT00503243 and Study 2, NCT00548574) were conducted in 517 adult patients with mildly to moderately active ulcerative colitis. The study population was primarily Caucasian (80%), had a mean age of 42 years (6% age 65 years or older), and was approximately 50% male. Both studies used LIALDA dosages of 2.4 g and 4.8 g administered once daily for 8 weeks, except in Study 1 the 2.4 g dosage was administered as two divided doses (i.e., 1.2 g twice daily). The primary efficacy endpoint in both trials was to compare the percentage of patients in remission after 8 weeks of treatment for the LIALDA treatment groups versus placebo. Remission was defined as an Ulcerative Colitis Disease Activity Index (UC-DAI) of ≤1, with scores of zero for rectal bleeding and for stool frequency, and a sigmoidoscopy score reduction of 1 point or more from baseline.

In both studies, the LIALDA dosages of 2.4 g and 4.8 g once daily demonstrated superiority over placebo in the primary efficacy endpoint (Table 6). Both LIALDA dosages also provided consistent benefit in secondary efficacy parameters, including clinical improvement, clinical remission, and sigmoidoscopic improvement. Both LIALDA dosages had similar efficacy profiles.

Table 6: Proportion of Adult Patients with Mildly to Moderately Active Ulcerative Colitis in Remission at Week 8 in Two Double-Blind Placebo-Controlled Induction Trials
Dose | Study 1 (n=262) n/N (%) | Study 2 (n=255) n/N (%)
LIALDA 2.4 g/day | 30/88 (34) | 34/84 (41)
LIALDA 4.8 g/day | 26/89 (29) | 35/85 (41)
Placebo | 11/85 (13) | 19/86 (22)

Maintenance of Remission

A multicenter, randomized, double-blind, active comparator study (Study 3, NCT00151892) was conducted in a total of 826 adult patients in remission from ulcerative colitis. Patients were randomized in a 1:1 ratio to receive either LIALDA 2.4 g administered once daily or another mesalamine delayed-release product administered as 0.8 g twice daily. The study population had a mean age of 45 years (8% age 65 years or older), were 52% male, and were primarily Caucasian (64%).

Maintenance of remission was assessed using a modified UC-DAI. For this trial, maintenance of remission was based on maintaining endoscopic remission defined as a modified UC-DAI endoscopy subscore of ≤1. An endoscopy subscore of 0 represented normal mucosal appearance with intact vascular pattern and no friability or granulation. For this trial the endoscopy score definition of 1 (mild disease) was modified such that it could include erythema, decreased vascular pattern, and minimal granularity; however, it could not include friability.

The proportion of patients who maintained remission at Month 6 in this study using LIALDA 2.4 g once daily (84%) was similar to the comparator (82%).

14.2 Pediatric Patients with Mildly to Moderately Active Ulcerative Colitis Weighing at Least 24 kg

A multicenter, randomized, double-blind, parallel-group study (NCT02093663) was conducted in pediatric patients aged 5 through 17 years with mildly to moderately active ulcerative colitis to determine the safety and effectiveness of LIALDA. The study consisted of two treatment phases, an initial 8-week phase and a 26-week phase. The overall population consisted of 105 patients, of whom 27 patients participated in both the 8-week and 26-week phases.

Each phase included two dosage arms and patients were randomized at the beginning of each phase in a 1:1 ratio, stratified by body weight group. Patients received a low or a high weight-based dosage of LIALDA in four weight groups. Because of the small number of patients in the lowest body weight group (0 in the 8-week phase and 3 in the 26-week phase), the safety and effectiveness of LIALDA in patients weighing less than 24 kg have not been established.

Patients were eligible for the initial 8-week phase if they had mildly to moderately active ulcerative colitis as defined by the UC-DAI score of at least 4 with an endoscopic subscore of 2 or 3.

In the 53 patients enrolled in the initial phase, the mean age and weight of patients was 14 years and 53 kg, the mean (SD) baseline UC-DAI score was 5.8 (1.8), 93% were white, and 59% were male. The primary endpoint was defined by the partial UC-DAI less than or equal to 1 (with rectal bleeding equal to 0, stool frequency less than or equal to 1, and Physician's Global Assessment [PGA] equal to 0). Of the 26 patients in the recommended LIALDA dosage arm, 65% achieved the primary endpoint after 8 weeks of treatment. During the initial 8-week phase, fewer patients who received the recommended LIALDA dosage were discontinued from the study due to ulcerative colitis (0/26, 0%) compared to patients who received a lower than recommended LIALDA dosage (8/27, 30%).

Patients who met the primary endpoint at 8 weeks were eligible to continue treatment in the 26-week phase. Patients were also eligible to enter the 26-week phase without having participated in the 8-week phase if they had a UC-DAI score of less than or equal to 2 with an endoscopic subscore of 0 or 1 (modified to exclude friability).

There were 87 patients enrolled in the 26-week phase. The mean age and weight of patients were 14 years and 54 kg; 97% were white and 55% were female. Of the 42 patients in the recommended LIALDA dosage arm, 55% achieved the primary endpoint, which was defined the same as in the 8-week phase. In the 26-week phase, the arm with a higher than recommended LIALDA dosage was not more effective and is not recommended [see Dosage and Administration (2)].

Other Endpoints

Clinical remission, defined by a Mayo stool frequency subscore equal to 0 or 1, Mayo rectal bleeding subscore equal to 0, and a Mayo endoscopic subscore equal to 0 or 1 (modified to exclude friability) or 0 on the UC-DAI, was determined for patients with available endoscopic assessment after completion of the 26-week phase. Patients without endoscopic data at week 26 were assumed not to have achieved clinical remission. Of the 42 patients in the recommended LIALDA dosage arm, 36% achieved clinical remission. Clinical remission could not be assessed in the initial 8-week phase because there were too few patients who underwent endoscopy.

16 HOW SUPPLIED/STORAGE AND HANDLING

LIALDA is available as red-brown, ellipsoidal, film-coated, delayed-release tablets containing 1.2 g mesalamine, and debossed on one side imprinted with S476.

NDC 54092-476-12 HDPE Bottle with a child-resistant closure of 120 delayed-release tablets.

STORAGE AND HANDLING

Store at room temperature 15°C to 25°C (59°F to 77°F); excursions permitted to 30°C (86°F).

See USP Controlled Room Temperature.

17 PATIENT COUNSELING INFORMATION

Renal Impairment

Inform patients that LIALDA may decrease their renal function, especially if they have known renal impairment or are taking nephrotoxic drugs, and periodic monitoring of renal function will be performed while they are on therapy. Advise patients to complete all blood tests ordered by their healthcare provider [see Warnings and Precautions (5.1)].

Mesalamine-Induced Acute Intolerance Syndrome and Other Hypersensitivity Reactions

Instruct patients to stop taking LIALDA and report to their healthcare provider if they experience new or worsening symptoms of acute intolerance syndrome (cramping, abdominal pain, bloody diarrhea, fever, headache, and rash) or other symptoms suggestive of mesalamine-induced hypersensitivity [see Warnings and Precautions (5.2, 5.3)].

Hepatic Failure

Advise patients with known liver disease to contact their healthcare provider if they experience signs or symptoms of worsening liver function [see Warnings and Precautions (5.4)].

Severe Cutaneous Adverse Reactions

Inform patients of the signs and symptoms of severe cutaneous adverse reactions. Instruct patients to stop taking LIALDA and report to their healthcare provider at first appearance of a severe cutaneous adverse reaction or other sign of hypersensitivity [see Warnings and Precautions (5.5)].

Upper Gastrointestinal Tract Obstruction

Advise patients to contact their healthcare provider if they experience signs and symptoms of upper gastrointestinal tract obstruction [see Warnings and Precautions (5.6)].

Photosensitivity

Advise patients with pre-existing skin conditions to avoid sun exposure, wear protective clothing, and use a broad-spectrum sunscreen when outdoors [see Warnings and Precautions (5.7)].

Nephrolithiasis

Instruct patients to drink an adequate amount of fluids during treatment in order to minimize the risk of kidney stone formation and to contact their healthcare provider if they experience signs or symptoms of a kidney stone (e.g., severe side or back pain, blood in the urine) [see Warnings and Precautions (5.8)].

Blood Disorders

Inform elderly patients and those taking azathioprine or 6-mercaptopurine of the risk for blood disorders and the need for periodic monitoring of complete blood cell counts and platelet counts while on therapy. Advise patients to complete all blood tests ordered by their healthcare provider [see Drug Interactions (7.2), Use in Specific Populations (8.5)].

Administration

Instruct patients:

- Swallow LIALDA tablets whole; do not split or crush.
- Take LIALDA tablets with food [see Clinical Pharmacology (12.3)].
- Urine may become discolored reddish-brown while taking LIALDA when it comes in contact with surfaces or water treated with hypochlorite-containing bleach. If discolored urine is observed, advise patients to observe their urine flow. Report to the healthcare provider only if urine is discolored on leaving the body, before contact with any surface or water (e.g., in the toilet).
- Drink an adequate amount of fluids [see Warnings and Precautions (5.8)].

Manufactured for Takeda Pharmaceuticals America, Inc., Lexington, MA 02421, USA by Cosmo S.p.A., Milan, Italy.

LIALDA® is a registered trademark of Nogra Pharma Ltd., Ireland used under license. By license of Nogra Pharma Limited, Dublin, Ireland.

© 2023 Takeda Pharmaceuticals U.S.A., Inc. All rights reserved.

PRINCIPAL DISPLAY PANEL - 1.2 g Tablet Bottle Label

ONCE-DAILY
NDC 54092-476-12

Lialda®
(mesalamine)
delayed release
tablets
1.2 g per tablet

Rx Only

120 Tablets

Takeda

PRINCIPAL DISPLAY PANEL - 1.2 g Tablet Bottle Carton

ONCE-DAILY
NDC 54092-476-02

Lialda®
(mesalamine)
delayed release tablets
1.2 g per tablet

Rx Only

1 carton of 12 bottles containing 120 tablets each

Takeda